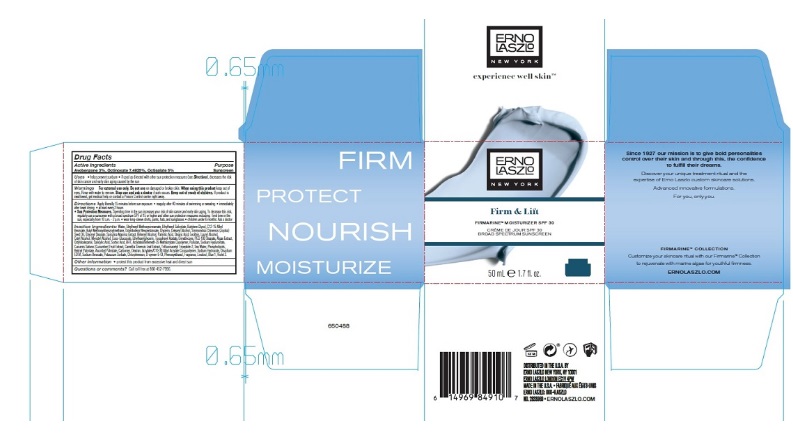 DRUG LABEL: Firmarine Moisturizer  SPF 30
NDC: 57913-2833 | Form: LOTION
Manufacturer: Erno Laszlo, Inc.
Category: otc | Type: HUMAN OTC DRUG LABEL
Date: 20251222

ACTIVE INGREDIENTS: AVOBENZONE 30 mg/1 mL; OCTINOXATE 75 mg/1 mL; OCTISALATE 50 mg/1 mL
INACTIVE INGREDIENTS: WATER; BUTYLENE GLYCOL; OCTYLDODECYL NEOPENTANOATE; ALKYL (C12-15) BENZOATE; GLYCERIN; JOJOBA OIL; GLYCERYL MONOSTEARATE; CETOSTEARYL ALCOHOL; DOCOSANOL; PALMITIC ACID; STEARIC ACID; LAURYL ALCOHOL; CETYL ALCOHOL; MYRISTYL ALCOHOL; COCO GLUCOSIDE; ETHYLHEXYLGLYCERIN; DIMETHICONE; PEG-100 STEARATE; SPIRULINA MAXIMA; CUCUMBER; GREEN TEA LEAF; .ALPHA.-TOCOPHEROL ACETATE; VITAMIN A PALMITATE; ASCORBYL PALMITATE; PULLULAN; HYALURONATE SODIUM; SODIUM CHLORIDE; SODIUM HYDROXIDE; EDETATE DISODIUM; O-CYMEN-5-OL; PHENOXYETHANOL; FD&C BLUE NO. 1; EXT. D&C VIOLET NO. 2

Firmarine™ Moisturizer SPF 30

Drug Facts

Active Ingredients

Avobenzone 3%, Octinoxate 7.5%, Octisalate 5%

Purpose

Sunscreen

Uses

- helps prevent sunburn
- if used as directed with other sun protection measures (see Directions), decreases the risk of skin cancer and early skin aging caused by the sun

Warnings

For external use only.

Do not useon damaged or broken skin.

WHEN USING

When using this productkeep out of eyes. Rinse with water to remove.

Stop use and ask a doctorif rash occurs.

Keep out of reach of children.If product is swallowed, get medical help or contact a Poison Control center right away.

Directions

Apply liberally 15 minutes before sun exposure

- reapply: after 40 minutes of swimming or sweating
- immediately after towel drying
- at least every 2 hours
- Sun Protection Measures.Spending time in the sun increases your risk of skin cancer and early skin aging. To decrease this risk, regularly use a sunscreen with a broad spectrum SPF of 15 or higher and other sun protection measures including: limit time in the sun, especially from 10 a.m. - 2 p.m.
  - wear long-sleeve shirts, pants, hats, and sunglasses
  - children under 6 months: Ask a doctor

Inactive Ingredients

Water, Butylene Glycol, Octyldodecyl Neopentanoate, C12-15 Alkyl Benzoate, Glycerin, Simmondsia Chinensis (Jojoba) Seed Oil, Glyceryl Stearate, Cetearyl Alcohol, Behenyl Alcohol, Palmitic Acid, Stearic Acid, Lecithin, Lauryl Alcohol, Cetyl Alcohol, Myristyl Alcohol, Coco-Glucoside, Ethylhexylglycerin, Dimethicone, PEG-100 Stearate, Spirulina Maxima Extract, Cucumis Sativus (Cucumber) Fruit Extract, Camellia Sinensis Leaf Extract, Phospholipids, Tocopheryl Acetate, Retinyl Palmitate, Ascorbyl Palmitate, Algae Extract, Pullulan, Sodium Hyaluronate, Trifluoroacetyl Tripeptide-2, Sea Water, Carbomer, Dextran, Acrylates/C10-30 Alkyl Acrylate Crosspolymer, Sodium Hydroxide, Disodium EDTA, O-Cymen-5-Ol, Phenoxyethanol, Fragrance, Blue 1, Ext Violet 2.

Other information

- protect this product from excessive heat and direct sun

Questions or comments?

Call toll free at 866-452-7956.

DISTRIBUTED IN U.S.A. BY ERNO LASZLO NEW YORK, NY 10001